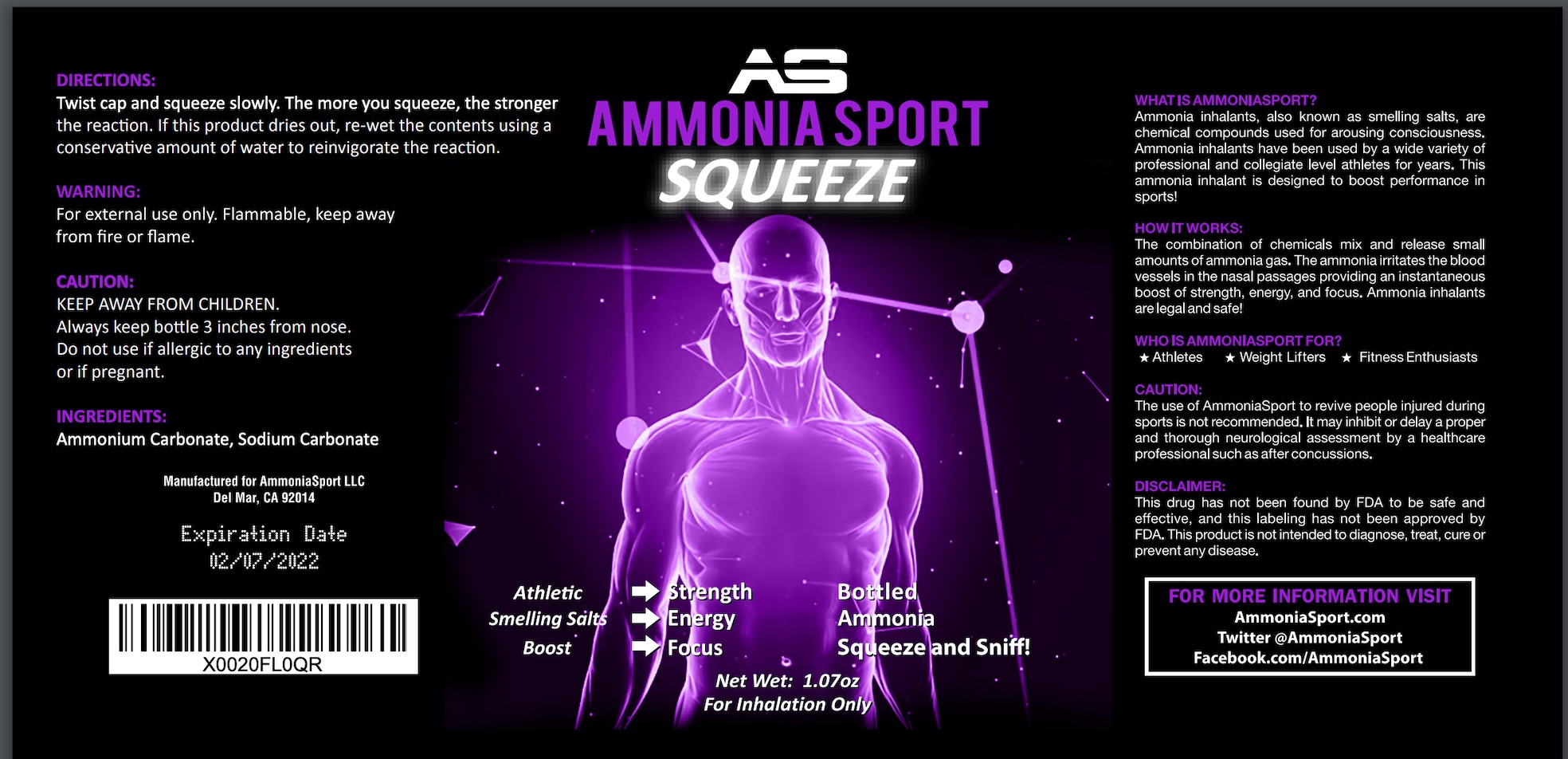 DRUG LABEL: AmmoniaSport SQUEEZE
NDC: 73395-198 | Form: LIQUID
Manufacturer: AmmoniaSport LLC
Category: otc | Type: HUMAN OTC DRUG LABEL
Date: 20200923

ACTIVE INGREDIENTS: AMMONIA 7 mg/1 mL
INACTIVE INGREDIENTS: WATER; SODIUM CARBONATE

AmmoniaSport Squeeze

Drug Facts

Active Ingredient

Ammonia 0.3%

Purpose

Respiratory Stimulant

Use

Respiratory stimulant used as a smelling salts to treat or prevent fainting.

Warnings

For external use only. Avoid eye contact with liquid vapors. Avoid inhaling more than a slight whiff. May cause irritation if excess is inhaled.

If pregnant or nursing a baby

seek the advice of a doctor before using this product.

Keep out of the reach of children

In case of accidental ingestion, seek professional assistance or contact a Poison Control Center right away.

Directions

Inhale a slight whiff to treat a "fainting spell"

Inactive Ingredients

Water, Sodium Carbonate

Other Information

Flammable: Keep away from spark, heat or flame. Keep tightly closed at room temperature not to exceed 30C (86F).

Questions or Comments?

1-800-662-3435

Label

31 ml NDC 73395-198